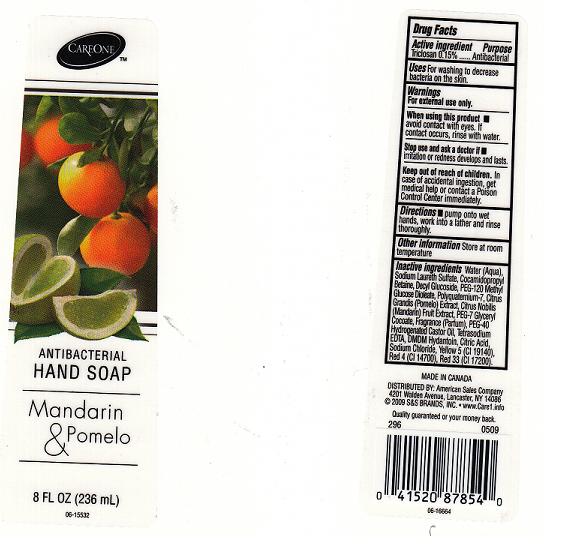 DRUG LABEL: ANTIBACTERIAL
NDC: 41520-293 | Form: LIQUID
Manufacturer: AMERICAN SALES COMPANY
Category: otc | Type: HUMAN OTC DRUG LABEL
Date: 20110401

ACTIVE INGREDIENTS: TRICLOSAN 0.15 mL/100 mL
INACTIVE INGREDIENTS: WATER; SODIUM LAURETH SULFATE; COCAMIDOPROPYL BETAINE; PEG-120 METHYL GLUCOSE DIOLEATE; POLYQUATERNIUM-7 (70/30 ACRYLAMIDE/DADMAC; 1600 KD); PUMMELO; CITRUS NOBILIS; POLYOXYL 40 HYDROGENATED CASTOR OIL; EDETATE SODIUM; DMDM HYDANTOIN; ANHYDROUS CITRIC ACID; SODIUM CHLORIDE; FD&C YELLOW NO. 5; FD&C RED NO. 4; D&C RED NO. 33; DECYL GLUCOSIDE; PEG-7 GLYCERYL COCOATE

DRUG FACTS

ACTIVE INGREDIENT

TRICLOSAN 0.15%

PURPOSE

ANTIBACTERIAL

USES

FOR WASHING TO DECREASE BACTERIA ON THE SKIN.

WARNINGS

FOR EXTERNAL USE ONLY.

WHEN USING THIS PRODUCT

AVOID CONTACT WITH EYES. IF CONTACT OCCURS, RINSE WITH WATER.

STOP USE AND ASK A DOCTOR IF

IF IRRITATION OR REDNESS DEVELOPS AND LASTS.

KEEP OUT OF REACH OF CHILDREN

IN CASE OF ACCIDENTAL INGESTION, GET MEDICAL HELP OR CONTACT A POISON CONTROL CENTER IMMEDIATELY.

DIRECTIONS

PUMP ONTO WET HANDS, WORK INTO A LATHER AND RINSE THOROUGHLY.

OTHER INFORMATION

STORE AT ROOM TEMPERATURE.

INACTIVE INGREDIENTS

WATER, SODIUM LAURETH SULFATE, COCAMIDOPROPYL BETAINE, DECYL GLUCOSIDE, PEG-120 METHYL GLUCOSE DIOLEATE, POLYQUATERNIUM-7, CITRUS GRANDIS (POMELO) EXTRACT, CITRUS NOBILIS (MANDARIN) FRUIT EXTRACT, PEG-7 GLYCERYL COCOATE, FRAGRANCE (PARFUM), PEG-40 HYDROGENATED CASTOR OIL, TETRASODIUM EDTA, DMDM HYDANTOIN, CITRIC ACID, SODIUM CHLORIDE, YELLOW 5 (CI 19140), RED 4 (CI 14700), RED 33 (CI 17200).